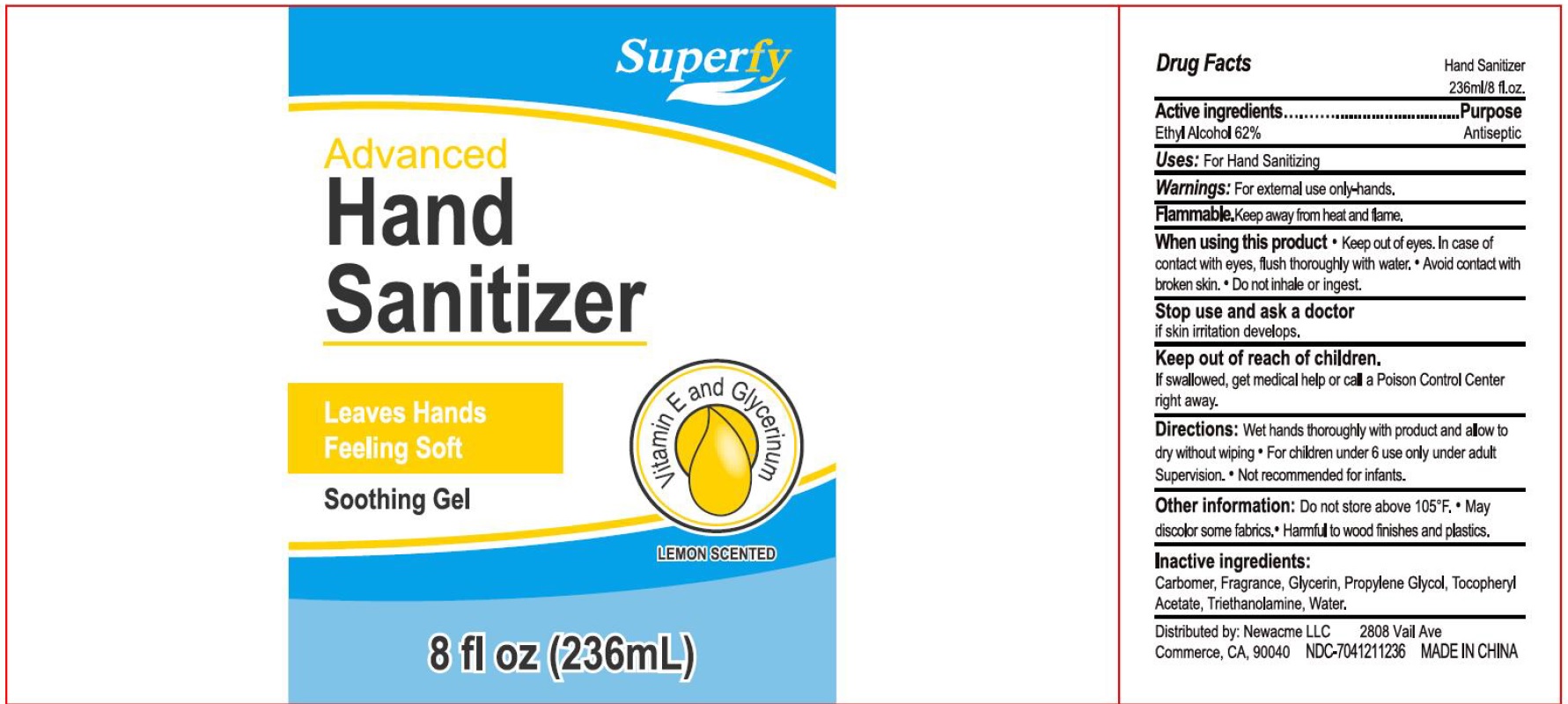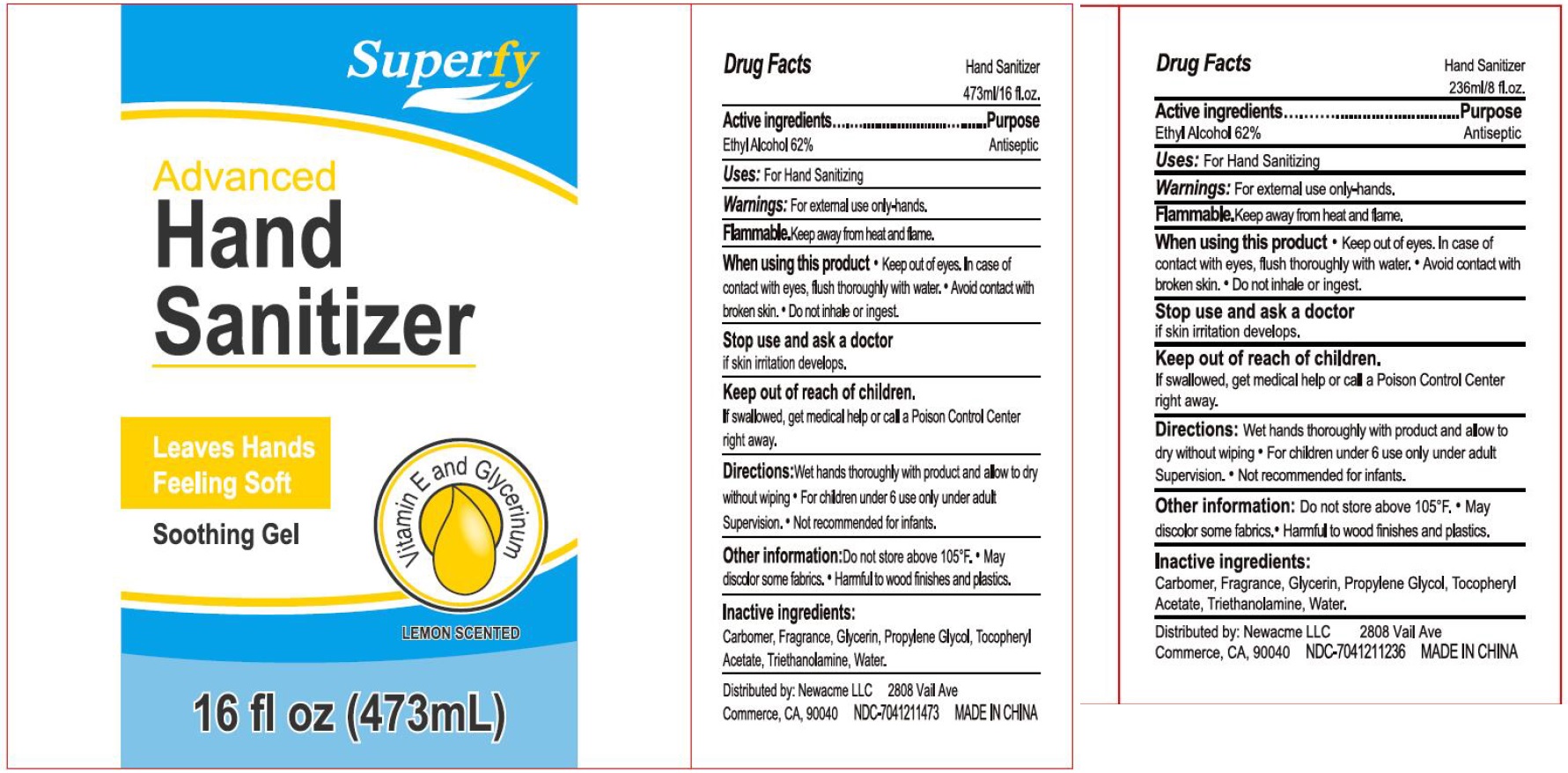 DRUG LABEL: Hand Sanitizer
NDC: 74341-191 | Form: GEL
Manufacturer: Newacme LLC
Category: otc | Type: HUMAN OTC DRUG LABEL
Date: 20220128

ACTIVE INGREDIENTS: ALCOHOL 0.62 mL/1 mL
INACTIVE INGREDIENTS: CARBOMER HOMOPOLYMER, UNSPECIFIED TYPE; GLYCERIN; PROPYLENE GLYCOL; .ALPHA.-TOCOPHEROL ACETATE; TROLAMINE; WATER

Hand Sanitizer

Active Ingredients

Ethyl Alcohol 62%

Purpose

Antiseptic

Uses:

For Hand Sanitizing

Warnings:

For external use only-hands.

Flammable. Keep away from heat and flame

When using this product

- Keep out of eyes. In case of contact with eyes, flush thoroughly with water.
- Avoid contact with broken skin.
- Do not inhale or ingest.

Stop use or ask a doctor

if skin irritation develops.

Keep out of reach of children.

If swallowed, get medical help or contact a Poison Control Center right away.

Directions:

- Wet hands thoroughly with a product and allow to dry without wiping
- For children under 6 use only under adult Supervision.
- Not recommended for infants.

Other information:

Do not store above 105oF. May discolor some fabrics. Harmful to wood finishes and plastics.

Inactive Ingredients:

Carbomer, Fragrance, Glycerin, Propylene Glycol, Tocopheryl ACetate, Triethanolamine, Water.